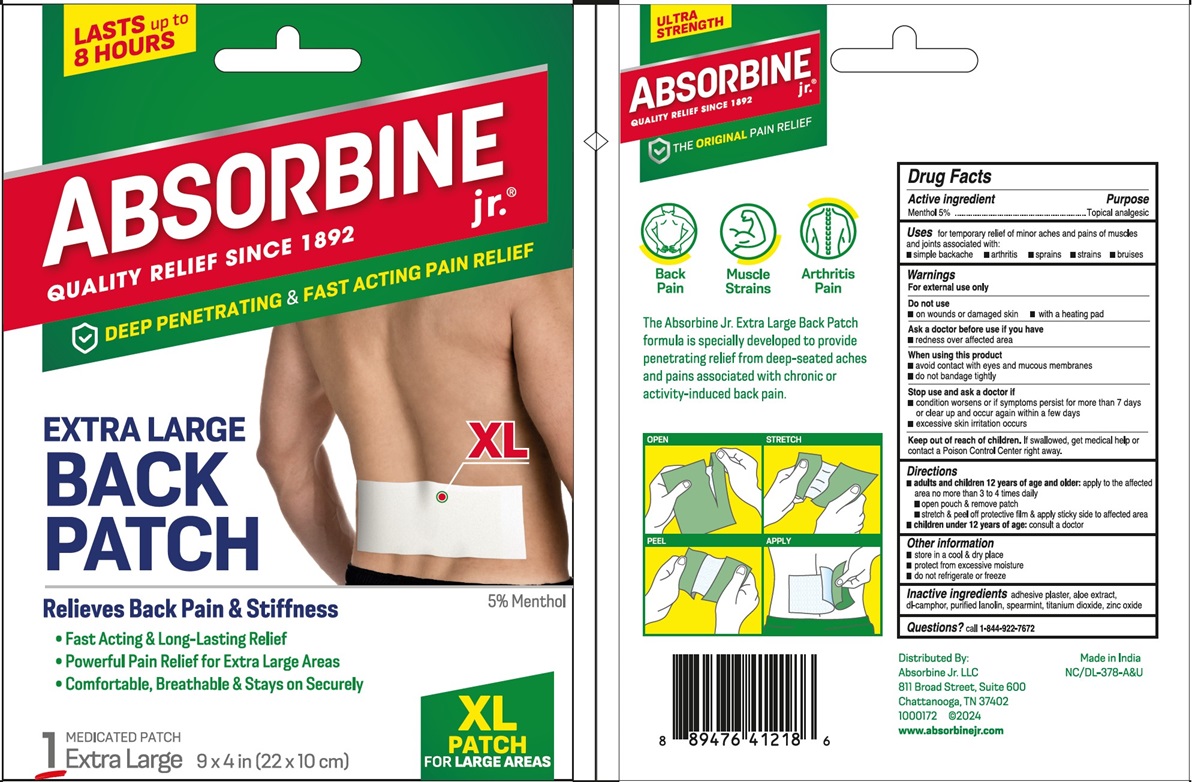 DRUG LABEL: ABSORBINE JR
NDC: 69693-412 | Form: PATCH
Manufacturer: Clarion Brands, LLC
Category: otc | Type: HUMAN OTC DRUG LABEL
Date: 20251223

ACTIVE INGREDIENTS: MENTHOL 5000 mg/1 h
INACTIVE INGREDIENTS: ALOE; CAMPHOR (SYNTHETIC); LANOLIN; SPEARMINT; TITANIUM DIOXIDE; ALUMINUM CHLOROHYDRATE; MINERAL OIL; SILICON DIOXIDE; ZINC OXIDE

Drug Facts

Active Ingredient

Active Ingredient | Purpose
Menthol 5% | Topical Analgesic

Uses

For temporary relief of minor aches and pains of muscles and joints associated with:

- simple backache
- arthritis
- sprains
- strains
- bruises

Warnings

For external use only.

Do not use

- on wounds or damaged skin
- with a heating pad

Ask a doctor before use if you have

- redness over affected area

When using this product

- avoid contact with eyes and mucous membranes
- do not bandage tightly

Stop use and ask a doctor if

- condition worsens or if symptoms persist for more than 7 days or clear up and occur again within a few days
- excessive skin irritation occurs

Keep out of reach of children.If swallowed, get medical help or contact a Poison Control Center right away.

Directions

- adults and children 12 years of age and older apply to the affected area no more than 3 to 4 times daily
- open pouch & remove patch
- peel off protective film and apply sticky side to affected area
- children under 12 years of age consult a doctor

Inactive ingredients

adhesive plaster, aloe extract, dl-camphor, purified lanolin, spearmint, titanium dioxide, zinc oxide

PRINCIPAL DISPLAY PANEL

Lasts up to 8 Hours!
Absorbine jr.®
QUALITY RELIEF SINCE 1892
DEEP PENETRATING & FAST ACTING PAIN RELIEF
EXTRA LARGE
BACK PATCH
XL
5% Menthol
Relieves Back Pain & Stiffness
• Fast Acting & Long-Lasting Relief
• Powerful Pain Relief for Extra Large Areas
• Comfortable, Breathable & Stays on Securely
Medicated Patch
1 EXTRA LARGE 9 × 4 in (22 × 10 cm)
XL
PATCH
FOR LARGE AREAS
ULTRA STRENGTH
Absorbine jr.®
QUALITY RELIEF SINCE 1892
THE ORIGINALPAIN RELIEF
• Back Pain
• Muscle Strains
• Arthritis Pain
The Absorbine Jr. Extra Large Back Patch
formula is specially developed to provide
penetrating relief from deep-seated aches
and pains associated with chronic or
activity-induced back pain.
Distributed by:
Absorbine Jr. LLC
811 Broad Street, Suite 600
Chattanooga, TN 37402
1000172 @2024
www.absorbinejr.com
Made in India
NC/DL-378-A&U